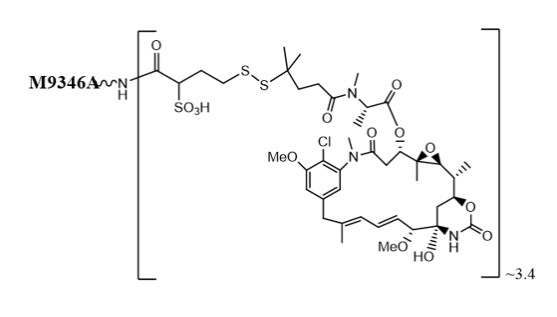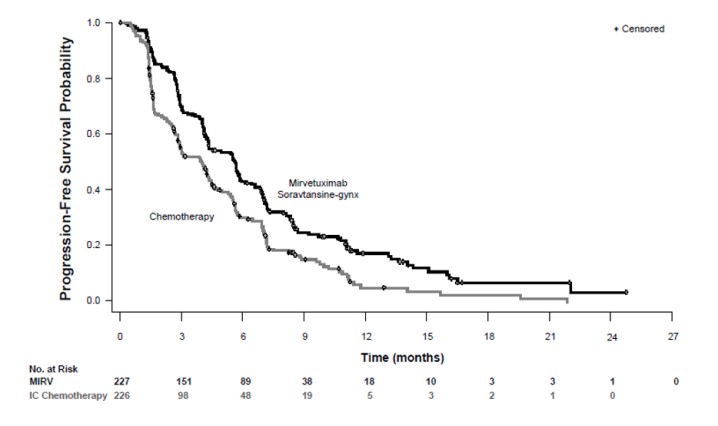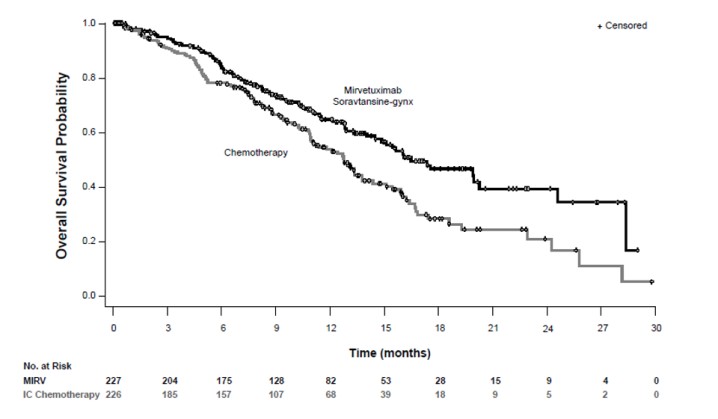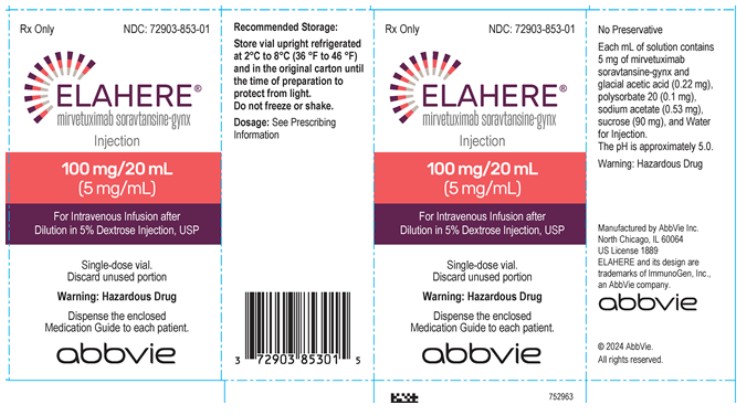 DRUG LABEL: ELAHERE
NDC: 72903-853 | Form: INJECTION, SOLUTION
Manufacturer: ImmunoGen, Inc.
Category: prescription | Type: HUMAN PRESCRIPTION DRUG LABEL
Date: 20250714

ACTIVE INGREDIENTS: MIRVETUXIMAB SORAVTANSINE 5 mg/1 mL
INACTIVE INGREDIENTS: ACETIC ACID 0.22 mg/1 mL; POLYSORBATE 20 0.1 mg/1 mL; SODIUM ACETATE 0.53 mg/1 mL; SUCROSE 90 mg/1 mL; WATER

HIGHLIGHTS OF PRESCRIBING INFORMATION

These highlights do not include all the information needed to use ELAHERE safely and effectively. See full prescribing information for ELAHERE.
ELAHERE® (mirvetuximab soravtansine-gynx) injection, for intravenous use.
Initial U.S. Approval: 2022

RECENT MAJOR CHANGES

Dosage and Administration (2.5) | 07/2025

WARNING: OCULAR TOXICITY

See full prescribing information for complete boxed warning.

- ELAHERE can cause severe ocular toxicities, including visual impairment, keratopathy, dry eye, photophobia, eye pain, and uveitis. (5.1, 6.1)
- Conduct an ophthalmic exam including visual acuity and slit lamp exam prior to initiation of ELAHERE, every other cycle for the first 8 cycles, and as clinically indicated. (2.3)
- Administer prophylactic artificial tears and ophthalmic topical steroids. (2.3, 5.1)
- Withhold ELAHERE for ocular toxicities until improvement and resume at the same or reduced dose. (2.4, 5.1)
- Discontinue ELAHERE for Grade 4 ocular toxicities. (2.4, 5.1)

1 INDICATIONS AND USAGE

ELAHERE is a folate receptor alpha (FRα)-directed antibody and microtubule inhibitor conjugate indicated for the treatment of adult patients with FRα positive, platinum-resistant epithelial ovarian, fallopian tube, or primary peritoneal cancer, who have received one to three prior systemic treatment regimens. Select patients for therapy based on an FDA-approved test. (1, 2.1)

2 DOSAGE AND ADMINISTRATION

- Administer ELAHERE as an intravenous infusion only after dilution in 5% Dextrose Injection, USP. ELAHERE is incompatible with normal saline. (2.5)
- The recommended dose of ELAHERE is 6 mg/kg adjusted ideal body weight administered as an intravenous infusion every 3 weeks until disease progression or unacceptable toxicity. (2.2)
- Premedicate with a corticosteroid, antihistamine, and antipyretic. (2.3)
- Premedicate with an antiemetic, ophthalmic topical steroids, and lubricating eye drops. (2.3, 5.1)
- See full Prescribing Information for preparation and administration instructions and dose modifications for adverse reactions. (2)

3 DOSAGE FORMS AND STRENGTHS

- Injection: 100 mg/20 mL (5 mg/mL) in a single-dose vial. (3)

4 CONTRAINDICATIONS

- None. (4)

5 WARNINGS AND PRECAUTIONS

- Pneumonitis: Withhold ELAHERE for persistent or recurrent Grade 2 pneumonitis and consider dose reduction. Permanently discontinue ELAHERE for Grade 3 or 4 pneumonitis. (2.4, 5.2)
- Peripheral Neuropathy: Monitor patients for new or worsening peripheral neuropathy. Withhold dosage, dose reduce, or permanently discontinue ELAHERE based on the severity of peripheral neuropathy. (2.4, 5.3)
- Embryo-Fetal Toxicity: ELAHERE can cause fetal harm. Advise of the potential risk to a fetus and to use effective contraception. (5.4, 8.1, 8.3)

6 ADVERSE REACTIONS

The most common (≥20 %) adverse reactions, including lab abnormalities, were increased aspartate aminotransferase, fatigue, increased alanine aminotransferase, blurred vision, nausea, increased alkaline phosphatase, diarrhea, abdominal pain, keratopathy, peripheral neuropathy, musculoskeletal pain, decreased lymphocytes, decreased platelets, decreased magnesium, decreased hemoglobin, dry eye, constipation, decreased leukocytes, vomiting, decreased albumin, decreased appetite, and decreased neutrophils. (6.1)

To report SUSPECTED ADVERSE REACTIONS, contact AbbVie at 1-800-633-9110 or FDA at 1-800-FDA-1088 or www.fda.gov/medwatch.

7 DRUG INTERACTIONS

Strong CYP3A4 Inhibitors: Closely monitor for ELAHERE adverse reactions. (7.1)

8 USE IN SPECIFIC POPULATIONS

- Lactation: Advise not to breastfeed. (8.2)
- Moderate or severe hepatic impairment: Avoid use. (8.7)

FULL PRESCRIBING INFORMATION

WARNING: OCULAR TOXICITY

- ELAHERE can cause severe ocular toxicities, including visual impairment, keratopathy, dry eye, photophobia, eye pain, and uveitis [see Warnings and Precautions (5.1) and Adverse Reactions (6.1)].
- Conduct an ophthalmic exam including visual acuity and slit lamp exam prior to initiation of ELAHERE, every other cycle for the first 8 cycles, and as clinically indicated [see Dosage and Administration (2.3)].
- Administer prophylactic artificial tears and ophthalmic topical steroids [see Dosage and Administration (2.3) and Warnings and Precautions (5.1)].
- Withhold ELAHERE for ocular toxicities until improvement and resume at the same or reduced dose [see Dosage and Administration (2.4) and Warnings and Precautions (5.1)].
- Discontinue ELAHERE for Grade 4 ocular toxicities [see Dosage and Administration (2.4) and Warnings and Precautions (5.1)].

1 INDICATIONS AND USAGE

ELAHERE® is indicated for the treatment of adult patients with folate receptor-alpha (FRα) positive, platinum-resistant epithelial ovarian, fallopian tube, or primary peritoneal cancer, who have received one to three prior systemic treatment regimens. Select patients for therapy based on an FDA-approved test [see Dosage and Administration (2.1)].

2 DOSAGE AND ADMINISTRATION

2.1 Patient Selection

Select patients for the treatment of platinum-resistant epithelial ovarian, fallopian tube, or primary peritoneal cancer with ELAHERE based on the presence of FRα tumor expression [see Indications & Usage (1) and Clinical Studies (14)] using an FDA-approved test.

Information on FDA-approved tests for the measurement of FRα tumor expression is available at http://www.fda.gov/CompanionDiagnostics.

2.2 Recommended Dosage

The recommended dosage of ELAHERE is 6 mg/kg adjusted ideal body weight (AIBW) administered once every 3 weeks (21-day cycle) as an intravenous infusion until disease progression or unacceptable toxicity [see Dosage and Administration (2.5)]. Dosing based on AIBW reduces exposure variability for patients who are either under or overweight.

The total dose of ELAHERE is calculated based on each patient’s AIBW using the following formula:

AIBW = Ideal Body Weight (IBW [kg]) + 0.4*(Actual weight [kg] – IBW)

Female IBW [kg] = 0.9*height[cm] – 92

2.3 Premedication and Required Eye Care

Premedication

Administer the premedications in Table 1 prior to each infusion of ELAHERE to reduce the incidence and severity of infusion related reactions (IRRs), nausea, and vomiting.

Table 1: Premedication Prior to Each ELAHERE Infusion
Premedication | Route of Administration | Examples (or equivalent) | Administration Time Prior to ELAHERE Infusion
Corticosteroid | intravenous | dexamethasone 10 mg
Antihistamine | oral or intravenous | diphenhydramine 25 mg to 50 mg | At least 30 minutes prior
Antipyretic | oral or intravenous | acetaminophen 325 mg to 650 mg
Antiemetic | oral or intravenous | 5-HT3 serotonin receptor antagonist or appropriate alternatives | Before each dose and thereafter as needed

Consider additional premedications including corticosteroids the day prior to ELAHERE administration for patients who experienced IRRs.

Ophthalmic Exams and Premedication

Ophthalmic Exam: Conduct an ophthalmic exam including visual acuity and slit lamp exam prior to initiation of ELAHERE, every other cycle for the first 8 cycles, and as clinically indicated.

Ophthalmic Topical Steroids: The use of ophthalmic topical steroids is recommended. The initial prescription and renewals of any corticosteroid medication should be made only after examination with a slit lamp. Administer one drop of ophthalmic topical steroids in each eye 6 times daily starting the day prior to each infusion until day 4; then administer one drop in each eye 4 times daily for days 5-8 of each cycle of ELAHERE [see Warnings and Precautions (5.1)].

Lubricating Eye Drops: The use of lubricating eye drops at least four times daily and as needed is recommended during treatment with ELAHERE. Instruct patients to use lubricating eye drops and advise to wait at least 10 minutes after ophthalmic topical steroid administration before instilling lubricating eye drops [see Warnings and Precautions (5.1)].

2.4 Dosage Modifications

Table 2 provides dose reduction levels and Table 3 provides dosage modifications for ELAHERE due to adverse reactions.

Table 2: Dosage Reduction Schedule
 | ELAHERE Dose Levels
First Dose Reduction | 5 mg/kg AIBW once every 3 weeks (21-day cycle)
Second Dose Reduction | 4 mg/kg AIBW once every 3 weeks (21-day cycle) *

* Permanently discontinue in patients who cannot tolerate 4 mg/kg AIBW.

Table 3: Dosage Modifications for Adverse Reactions
Adverse Reaction | Severity of Adverse Reaction* | Dosage Modification
 | Nonconfluent superficial keratitis | Monitor.
Keratitis/Keratopathy [see Warnings and Precautions (5.1) and Adverse Reactions (6.1)] | Confluent superficial keratitis, a cornea epithelial defect, or 3-line or more loss in best corrected visual acuity | Withhold until improved or resolved, then maintain at same dose level or consider dose reduction.
 | Corneal ulcer or stromal opacity or best corrected distance visual acuity 20/200 or worse | Withhold until improved or resolved, then reduce by one dose level.
 | Corneal perforation | Permanently discontinue.
 | Grade 1/ Rare cell in anterior chamber | Monitor.
Uveitis [see Warnings and Precautions (5.1) and Adverse Reactions (6.1)] | Grade 2/ 1-2+ Cell or Flare in anterior chamber | Withhold until Grade 1 or less, then maintain dose at same dose level.
 | Grade 3/ 3+ Cell or Flare in anterior chamber | Withhold until Grade 1 or less, then reduce dose by one dose level.
 | Grade 4/ Hypopyon | Permanently discontinue.
 | Grade 1 | Monitor.
Pneumonitis [see Warnings and Precautions (5.2) and Adverse Reactions (6.1)] | Grade 2 | Withhold until Grade 1 or less, then maintain at same dose level or consider dose reduction.
 | Grade 3 or 4 | Permanently discontinue.
Peripheral Neuropathy [see Warnings and Precautions (5.3) and Adverse Reactions (6.1)] | Grade 2 | Withhold until Grade 1 or less, then reduce by one dose level.
 | Grade 3 or 4 | Permanently discontinue.
 | Grade 1 | Maintain infusion rate.
Infusion-Related Reactions/Hypersensitivity [see Adverse Reactions (6.1)] | Grade 2 | - Interrupt infusion and administer supportive treatment. - After recovery from symptoms, resume the infusion at 50% of the previous rate, and if no further symptoms appear, increase rate as appropriate until infusion is completed [see Dosage and Administration (2.5)]. - Administer additional premedication for future cycles [see Dosage and Administration (2.3)].
 | Grade 3 or 4 | - Immediately stop infusion and administer supportive treatment. - Advise patient to seek emergency treatment and immediately notify their healthcare provider if the infusion-related symptoms recur. - Permanently discontinue.
Hematological [see Adverse Reactions (6.1)] | Grade 3 or 4 | Withhold until Grade 1 or less, then resume at one lower dose level.
Other Adverse Reactions | Grade 3 | Withhold until Grade 1 or less, then resume at one lower dose level.
[see Adverse Reactions (6.1)] | Grade 4 | Permanently discontinue.

* Unless otherwise specified, National Cancer Institute Common Terminology Criteria for Adverse Events (NCI CTCAE) version 5.0.

2.5 Instructions for Preparation and Administration

Preparation

- ELAHERE is a hazardous drug. Follow applicable special handling and disposal procedures^1.
- Calculate the dose (mg) (based on the patient’s AIBW), total volume (mL) of solution required, and the number of vials of ELAHERE needed [see Recommended Dosage (2.2) and Dose Modifications (2.4)]. More than one vial will be needed for a full dose.
- Remove the vials of ELAHERE from the refrigerator and allow to warm to room temperature.
- Parenteral drug products should be inspected visually for particulate matter and discoloration prior to administration, whenever solution and container permit. ELAHERE is a clear to slightly opalescent, colorless solution.
- Gently swirl and inspect each vial prior to withdrawing the calculated dose volume of ELAHERE. Do not shake the vial.
- Using aseptic technique, withdraw the calculated dose volume of ELAHERE for subsequent dilution.
- ELAHERE contains no preservatives and is intended for single-dose only. Discard any unused drug remaining in the vial.

Dilution

- ELAHERE must be diluted prior to administration with 5% Dextrose Injection, USP to a final concentration of 1 mg/mL to 2 mg/mL.
- ELAHERE is incompatible with 0.9% Sodium Chloride Injection. ELAHERE must not be mixed with any other drugs or intravenous fluids.
- Determine the volume of 5% Dextrose Injection, USP required to achieve the final diluted drug concentration. Either remove excess 5% Dextrose Injection, USP from a prefilled intravenous bag or add the calculated volume of 5% Dextrose Injection, USP to a sterile empty intravenous bag. Then add the calculated dose volume of ELAHERE to the intravenous bag.
- Gently mix the diluted drug solution by slowly inverting the bag several times to assure uniform mixing. Do not shake or agitate.

• If the diluted infusion solution is not used immediately, store solution either at ambient temperature [(18°C to 25°C (64.4°F to 77°F)] for no more than 8 hours (including infusion time), or under refrigeration at 2°C to 8°C (36°F to 46°F) for no more than 24 hours. If refrigerated, allow the infusion bag to reach room temperature prior to administration. After refrigeration, administer diluted infusion solutions within 8 hours (including infusion time).

- Do not freeze prepared infusion solution.

Administration

- Inspect the ELAHERE intravenous infusion bag visually for particulate matter and discoloration prior to administration.
- Administer pre-medications prior to ELAHERE administration [see Premedication and Prophylactic Regimen (2.3)].
- Administer ELAHERE as an intravenous infusion only, using a 0.2 or 0.22 µm polyethersulfone (PES) in-line filter. Do not substitute other membrane materials.
- Administer the initial dose as an intravenous infusion at the rate of 1 mg/min. If well tolerated after 30 minutes at 1 mg/min, the infusion rate can be increased to 3 mg/min. If well tolerated after 30 minutes at 3 mg/min, the infusion rate can be increased to 5 mg/min.
- If no infusion-related reactions occur with the previous dose, subsequent infusions should be started at the maximally tolerated rate and may be increased up to a maximum infusion rate of 5 mg/min, as tolerated.
- Following the infusion, flush the intravenous line with 5% Dextrose Injection, USP to ensure delivery of the full dose. Do not use any other intravenous fluids for flushing.

3 DOSAGE FORMS AND STRENGTHS

Injection: 100 mg/20 mL (5 mg/mL) clear to slightly opalescent, colorless solution in a single-dose vial.

4 CONTRAINDICATIONS

None.

5 WARNINGS AND PRECAUTIONS

5.1 Ocular Disorders

ELAHERE can cause severe ocular adverse reactions, including visual impairment, keratopathy (corneal disorders), dry eye, photophobia, eye pain, and uveitis.

Ocular adverse reactions occurred in 59% of patients with ovarian cancer treated with ELAHERE. Eleven percent (11%) of patients experienced Grade 3 ocular adverse reactions, including blurred vision, keratopathy (corneal disorders), dry eye, cataract, photophobia, and eye pain; two patients (0.3%) experienced Grade 4 events (keratopathy and cataract). The most common (≥5%) ocular adverse reactions were blurred vision (48%), keratopathy (36%), dry eye (27%), cataract (16%), photophobia (14%), and eye pain (10%). [see Adverse Reactions (6.1)].

The median time to onset for first ocular adverse reaction was 5.1 weeks (range: 0.1 to 68.6). Of the patients who experienced ocular events, 53% had complete resolution; 38% had partial improvement (defined as a decrease in severity by one or more grades from the worst grade) at last follow up. Ocular adverse reactions led to permanent discontinuation of ELAHERE in 1% of patients.

Premedication and use of lubricating and ophthalmic topical steroid eye drops during treatment with ELAHERE are recommended [see Dosage and Administration (2.3)]. Advise patients to avoid use of contact lenses during treatment with ELAHERE unless directed by a healthcare provider.

Refer patients to an eye care professional for an ophthalmic exam including visual acuity and slit lamp exam prior to treatment initiation, every other cycle for the first 8 cycles, and as clinically indicated. Promptly refer patients to an eye care professional for any new or worsening ocular signs and symptoms.

Monitor for ocular toxicity and withhold, reduce, or permanently discontinue ELAHERE based on severity and persistence of ocular adverse reactions. [see Dosage and Administration (2.4)].

5.2 Pneumonitis

Severe, life-threatening, or fatal interstitial lung disease (ILD), including pneumonitis, can occur in patients treated with ELAHERE.

Pneumonitis occurred in 10% of patients treated with ELAHERE, including 1% with Grade 3 events and 1 patient (0.1%) with a Grade 4 event. One patient (0.1%) died due to respiratory failure in the setting of pneumonitis and lung metastases. One patient (0.1%) died due to respiratory failure of unknown etiology.

Pneumonitis led to permanent discontinuation of ELAHERE in 3% of patients.

Monitor patients for pulmonary signs and symptoms of pneumonitis, which may include hypoxia, cough, dyspnea, or interstitial infiltrates on radiologic exams. Infectious, neoplastic, and other causes for such symptoms should be excluded through appropriate investigations. Withhold ELAHERE for patients who develop persistent or recurrent Grade 2 pneumonitis until symptoms resolve to ≤ Grade 1 and consider dose reduction. Permanently discontinue ELAHERE in all patients with Grade 3 or 4 pneumonitis [see Dosage and Administration (2.4)]. Patients who are asymptomatic may continue dosing of ELAHERE with close monitoring.

5.3 Peripheral Neuropathy

Peripheral neuropathy occurred in 36% of patients with ovarian cancer treated with ELAHERE across clinical trials; 3% of patients experienced Grade 3 peripheral neuropathy. Peripheral neuropathy adverse reactions included peripheral neuropathy (20%), peripheral sensory neuropathy (9%), paraesthesia (6%), neurotoxicity (3%), hypoesthesia (1%), peripheral motor neuropathy (0.9%), polyneuropathy (0.3%), and peripheral sensorimotor neuropathy (0.1%).

The median time to onset of peripheral neuropathy was 5.9 weeks (range 0.1 to 126.7). Of the patients who experienced peripheral neuropathy, 23% had complete resolution and 12% had partial improvement (defined as a decrease in severity by one or more grades from the worst grade) at last follow up. Peripheral neuropathy led to discontinuation of ELAHERE in 0.7% of patients.

Monitor patients for signs and symptoms of neuropathy, such as paresthesia, tingling or a burning sensation, neuropathic pain, muscle weakness, or dysesthesia. For patients experiencing new or worsening peripheral neuropathy, withhold dosage, dose reduce, or permanently discontinue ELAHERE based on the severity of peripheral neuropathy [see Dosage and Administration (2.4)].

5.4 Embryo-Fetal Toxicity

Based on its mechanism of action, ELAHERE can cause embryo-fetal harm when administered to a pregnant woman because it contains a genotoxic compound (DM4) and affects actively dividing cells.

Advise pregnant women of the potential risk to a fetus. Advise females of reproductive potential to use effective contraception during treatment with ELAHERE and for 7 months after the last dose [see Use in Specific Populations (8.1, 8.3)].

6 ADVERSE REACTIONS

The following adverse reactions are discussed elsewhere in the labeling:

- Ocular Disorders [see Warnings and Precautions (5.1)].
- Pneumonitis [see Warnings and Precautions (5.2)].
- Peripheral Neuropathy [see Warnings and Precautions (5.3)].

6.1 Clinical Trials Experience

Because clinical trials are conducted under widely varying conditions, adverse reaction rates observed in the clinical trials of a drug cannot be directly compared to rates in the clinical trials of another drug and may not reflect the rates observed in practice.

The pooled safety population described in Warnings and Precautions reflect exposure to ELAHERE in 682 patients with epithelial ovarian, fallopian tube, or primary peritoneal cancer at 6 mg/kg AIBW administered intravenously once every 3 weeks until disease progression or unacceptable toxicity in Study 0416, Study 0417, Study 0403 (NCT02631876), and Study 0401 (NCT01609556). The median duration of treatment was 4.4 months (range: 1.0 to 30.0). In the pooled safety population, the most common (≥20%) adverse reactions, including laboratory abnormalities, were increased aspartate aminotransferase, fatigue, increased alanine aminotransferase, blurred vision, nausea, increased alkaline phosphatase, diarrhea, abdominal pain, keratopathy, peripheral neuropathy, musculoskeletal pain, decreased lymphocytes, decreased platelets, decreased magnesium, decreased hemoglobin, dry eye, constipation, decreased leukocytes, vomiting, decreased albumin, decreased appetite, and decreased neutrophils.

Epithelial Ovarian, Fallopian Tube, or Primary Peritoneal Cancer

Study 0416

The safety of ELAHERE was evaluated in Study 0416, a multicenter, open-label, active-controlled, randomized, two-arm, study in patients (n=453) with platinum-resistant epithelial ovarian, fallopian tube, or primary peritoneal cancer [see Clinical Studies (14)]. Patients received ELAHERE 6 mg/kg AIBW once every 3 weeks until disease progression or unacceptable toxicity. The median duration of treatment was 5 months (range: 0.69 to 27.4).

Serious adverse reactions occurred in 24% of patients treated with ELAHERE. The most common (≥2%) serious adverse reactions were intestinal obstruction (5%), abdominal pain (3%), and pleural effusion (3%). Fatal adverse reactions occurred in 3% of patients, including intestinal obstruction, dyspnea in the setting of subileus, neutropenic sepsis, cardiopulmonary failure, respiratory failure, ischemic stroke, and pulmonary embolus.

Permanent discontinuation of ELAHERE due to adverse reactions occurred in 9% of patients. The most common (≥1%) adverse reactions leading to permanent discontinuation were pneumonitis (2%), blurred vision (1%), and peripheral neuropathy (1%).

Dosage delays of ELAHERE due to an adverse reaction occurred in 54% of patients treated with ELAHERE. Adverse reactions which required dosage delays in ≥3% of patients included blurred vision (22%), keratopathy (19%), dry eye (7%), neutropenia (6%), pneumonitis (6%), photophobia (5%), cataract (4%), and peripheral neuropathy (4%).

Dose reductions of ELAHERE due to an adverse reaction occurred in 34% of patients. Adverse reactions which required dose reductions in ≥3% of patients included blurred vision (14%), keratopathy (10%), peripheral neuropathy (6%), and dry eye (5%).

Tables 4 and 5 summarize adverse reactions and laboratory abnormalities, respectively, occurring in ≥10% of patients who received ELAHERE in Study 0416.

Table 4: Adverse Reactions Occurring in ≥10% of Patients with Epithelial Ovarian, Fallopian Tube, or Primary Peritoneal Cancer Who Received ELAHERE in Study 0416
Adverse Reaction | ELAHERE (n=218) |  | Chemotherapy¥ (n=207)
 | All Grades (%) | Grades 3-4 (%) | All Grades (%) | Grades 3-4 (%)
Gastrointestinal disorders
Abdominal pain* | 34 | 3 | 23 | 2
Diarrhea | 29 | 1 | 17 | 0.5
Constipation | 27 | 0 | 19 | 1
Nausea | 27 | 2 | 29 | 2
Vomiting | 18 | 3 | 18 | 1
Eye disorders
Blurred vision※ | 45 | 9 | 3 | 0
Keratopathy† | 37 | 11 | 0 | 0
Dry eye‡ | 29 | 3 | 5 | 0
Photophobia | 18 | 0.5 | 0.5 | 0
Cataract˄ | 16 | 3 | 0.5 | 0
General disorders and administration site conditions
Fatigue⸙ | 47 | 3 | 41 | 7
Nervous system disorders
Peripheral neuropathy¶ | 37 | 4 | 23 | 4
Headache | 14 | 0 | 10 | 0
Musculoskeletal and connective tissue disorders
Musculoskeletal pain♦ | 31 | 1 | 21 | 2
Metabolism and nutrition disorders
Decreased appetite | 18 | 1 | 14 | 1
Respiratory, thoracic, and mediastinal disorders
Pneumonitis± | 10 | 0.5 | 0.5 | 0

¥ Chemotherapy: paclitaxel, pegylated liposomal doxorubicin (PLD), topotecan.

※ Blurred vision includes vision blurred, vitreous floaters, visual acuity reduced, diplopia, accommodation disorder, and visual impairment.

† Keratopathy includes corneal disorder, corneal epithelial microcysts, keratitis, keratopathy, corneal deposits, punctate keratitis, and corneal opacity.

‡ Dry eye includes dry eye and lacrimation increased.

˄ Cataract includes cataract and cataract nuclear.

⸙ Fatigue includes fatigue and asthenia.

* Abdominal pain includes abdominal pain, abdominal pain upper, abdominal pain lower, and abdominal discomfort.

¶ Peripheral neuropathy includes neuropathy peripheral, peripheral sensory neuropathy, peripheral motor neuropathy, paresthesia, hypoesthesia, polyneuropathy, neurotoxicity, and peripheral sensorimotor neuropathy.

♦ Musculoskeletal pain includes back pain, myalgia, neck pain, arthralgia, musculoskeletal pain, non-cardiac chest pain, bone pain, pain in extremity, musculoskeletal stiffness, musculoskeletal chest pain, and musculoskeletal discomfort.

± Pneumonitis includes pneumonitis, interstitial lung disease, respiratory failure, and organizing pneumonia.

Clinically relevant adverse reactions occurring in <10% of patients who received ELAHERE in Study 0416 included infusion related reactions/hypersensitivity (8%).

Table 5: Select Laboratory Abnormalities ≥10% for All Grades, in Patients Who Received ELAHERE in Study 0416
Laboratory Abnormality | ELAHERE (n=218) |  | Chemotherapy (n=207)
 | All Grades % | Grades 3-4 % | All Grades % | Grades 3-4 %
Liver Function Tests
Increased aspartate aminotransferase | 57 | 0 | 14 | 0
Increased alanine aminotransferase | 38 | 1 | 15 | 1
Increased alkaline phosphatase | 30 | 1 | 13 | 1
Chemistry
Decreased albumin | 21 | 1 | 27 | 2
Decreased magnesium | 21 | 1 | 29 | 2
Decreased sodium | 16 | 0 | 18 | 0
Decreased potassium | 15 | 1 | 11 | 1
Increased calcium | 12 | 0 | 5 | 0
Decreased bicarbonate | 11 | 0 | 11 | 0
Increased creatinine | 10 | 0 | 11 | 0
Hematology*
Decreased lymphocytes | 27 | 3 | 42 | 11
Decreased leukocytes | 23 | 1 | 53 | 10
Decreased neutrophils | 22 | 1 | 45 | 17
Decreased hemoglobin | 18 | 1 | 63 | 8
Decreased platelets | 17 | 1 | 20 | 5

* The denominator used to calculate the rate varied from 63 to 214 (ELAHERE); 63 to 194 (IC Chemo) based on the number of patients with a baseline value and at least one post-treatment value.

Study 0417

The safety of ELAHERE was evaluated in Study 0417, a single-arm, open-label study in patients (n=106) with platinum-resistant epithelial ovarian, fallopian tube, or primary peritoneal cancer [see Clinical Studies (14)]. Patients received ELAHERE 6 mg/kg AIBW once every 3 weeks until disease progression or unacceptable toxicity. The median duration of treatment was 4.2 months (range: 0.7 to 13.3).

Serious adverse reactions occurred in 31% of patients treated with ELAHERE. The most common (≥2%) serious adverse reactions were intestinal obstruction (8%), ascites (4%), infection (3%), and pleural effusion (3%). Fatal adverse reactions occurred in 2% of patients, including small intestinal obstruction (1%) and pneumonitis (1%).

Permanent discontinuation of ELAHERE due to adverse reactions occurred in 11% of patients. The most common (≥2%) adverse reactions leading to permanent discontinuation were intestinal obstruction (2%) and thrombocytopenia (2%). One patient (0.9%) permanently discontinued ELAHERE due to visual impairment (unilateral decrease to BCVA ≤ 20/200 that resolved to baseline after discontinuation).

Dosage delays of ELAHERE due to an adverse reaction occurred in 39% of patients treated with ELAHERE. Adverse reactions which required dosage delays in ≥3% of patients included blurred vision (15%), keratopathy (11%), neutropenia (6%), dry eye (5%), cataracts (3%), and increased gamma-glutamyltransferase (3%).

Dose reductions of ELAHERE due to an adverse reaction occurred in 20% of patients. Adverse reactions which required dose reductions in ≥3% of patients included blurred vision (9%) and keratopathy (7%).

Table 6 summarizes the adverse reactions (≥10%) in patients treated with ELAHERE in Study 0417.

Table 6: Adverse Reactions (≥10%) in Patients with Epithelial Ovarian, Fallopian Tube, or Primary Peritoneal Cancer Who Received ELAHERE in Study 0417
Adverse Reaction | All Grades N=106 (%) | Grade 3-4 N=106 (%)
Eye disorders
Blurred Vision※ | 50 | 7
Keratopathy† | 37 | 9
Dry eye‡ | 27 | 2
Cataract | 18 | 3
Photophobia | 17 | 0
Eye pain§ | 10 | 0
General disorders
Fatigue | 49 | 3
Gastrointestinal disorders
Nausea | 40 | 0
Abdominal pain* | 36 | 7
Diarrhea | 31 | 3
Constipation | 30 | 1
Vomiting | 19 | 0
Abdominal distension | 11 | 0
Nervous system disorders
Peripheral neuropathy¶ | 33 | 2
Metabolism and nutrition disorders
Decreased appetite | 18 | 1
Musculoskeletal and connective tissue disorders
Arthralgia | 17 | 0
Myalgia | 10 | 0
Respiratory, thoracic, and mediastinal disorders
Dyspnea^ | 12 | 0

※ Blurred vision includes vision blurred, vitreous floaters, visual acuity reduced, diplopia, presbyopia, accommodation disorder, visual impairment, and refraction disorder.

† Keratopathy includes corneal disorder, corneal epithelial microcysts, corneal epithelial defect, keratitis, keratopathy, corneal deposits, and punctate keratitis.

‡ Dry eye includes dry eye and lacrimation increased.

§ Eye pain includes eye pain and ocular discomfort.

⸙ Fatigue includes fatigue and asthenia.

* Abdominal pain includes abdominal pain, abdominal pain upper, abdominal pain lower, and abdominal discomfort.

¶ Peripheral neuropathy includes neuropathy peripheral, peripheral sensory neuropathy, peripheral motor neuropathy, paresthesia, hypoesthesia, polyneuropathy, and neurotoxicity.

^ Dyspnea includes dyspnea and exertional dyspnea.

Clinically relevant adverse reactions occurring in <10% of patients who received ELAHERE in Study 0417 included infusion related reactions/hypersensitivity (9%), pneumonitis (8%), and uveitis (1%).

Table 7 summarizes the laboratory abnormalities in Study 0417.

Table 7: Select Laboratory Abnormalities ≥10% for All Grades, or ≥2% for Grades 3-4 in Patients Who Received ELAHERE
Laboratory Abnormality | ELAHERE*
 | All Grades (%) | Grade 3-4 (%)
Liver Function Tests
Increased aspartate aminotransferase | 50 | 2
Increased alanine aminotransferase | 39 | 2
Increased alkaline phosphatase | 30 | 1
Hematology*
Decreased lymphocytes | 35 | 7
Decreased leukocytes | 26 | 1
Decreased neutrophils | 26 | 3
Decreased hemoglobin | 25 | 3
Decreased platelets | 18 | 2
Chemistry
Decreased albumin | 31 | 1
Decreased magnesium | 27 | 2
Increased creatinine | 16 | 0
Decreased potassium | 15 | 4

* The denominator used to calculate the rate varied from 98 to 101 based on the number of patients with a baseline value and at least one post-treatment value.

Immunogenicity: Anti-Drug Antibody-Associated Adverse Reactions In studies 0416, 0417, 0401, and 0403 in patients with epithelial ovarian, fallopian tube, or primary peritoneal cancer who received ELAHERE at 6 mg/kg AIBW administered intravenously once every 3 weeks, 9% (57/626) developed anti-drug antibodies. Infusion reactions (including bronchospasm, erythema, eyelid erythema, flushing, hypersensitivity, periorbital edema, rash, allergic rhinitis, face edema) occurred in 26% (15/57) of patients with anti-drug antibodies and in 7% (41/569) who did not develop anti-drug antibodies [see Clinical Pharmacology (12.6)].

7 DRUG INTERACTIONS

7.1 Effects of Other Drugs on ELAHERE

Strong CYP3A4 Inhibitors

DM4 is a CYP3A4 substrate. Concomitant use of ELAHERE with strong CYP3A4 inhibitors may increase unconjugated DM4 exposure [see Clinical Pharmacology (12.3)], which may increase the risk of ELAHERE adverse reactions [see Adverse Reactions (6)]. Closely monitor patients for adverse reactions with ELAHERE when used concomitantly with strong CYP3A4 inhibitors [see Warnings and Precautions (5)].

8 USE IN SPECIFIC POPULATIONS

8.1 Pregnancy

Risk Summary

Based on its mechanism of action, ELAHERE can cause embryo-fetal harm when administered to a pregnant woman because it contains a genotoxic compound (DM4) and affects actively dividing cells [see Clinical Pharmacology (12.1), Nonclinical Toxicology (13.1)]. Human immunoglobulin G (IgG) is known to cross the placental barrier; therefore, ELAHERE has the potential to be transmitted from the mother to the developing fetus. There are no available human data on ELAHERE use in pregnant women to inform a drug-associated risk. No reproductive or developmental animal toxicity studies were conducted with mirvetuximab soravtansine-gynx. Advise patients of the potential risk to a fetus.

The estimated background risk of major birth defects and miscarriage for the indicated population is unknown. In the U.S. general population, the estimated background risk of major birth defects and miscarriage in clinically recognized pregnancies is 2-4% and 15-20%, respectively.

Data

Animal Data: No reproductive or developmental animal toxicity studies have been conducted with mirvetuximab soravtansine-gynx. The cytotoxic component of ELAHERE, DM4, disrupts microtubule function, is genotoxic, and can be toxic to actively dividing cells, suggesting it has the potential to cause embryotoxicity and teratogenicity.

8.2 Lactation

Risk Summary

There are no data on the presence of mirvetuximab soravtansine-gynx in human milk or the effects on the breastfed child or milk production. Because of the potential for serious adverse reactions in a breastfed child, advise women not to breastfeed during treatment with ELAHERE and for 1 month after the last dose.

8.3 Females and Males of Reproductive Potential

ELAHERE can cause embryo-fetal harm when administered to a pregnant woman [see Use in Specific Populations (8.1)].

Pregnancy Testing

Verify pregnancy status in females of reproductive potential prior to initiating ELAHERE.

Contraception

Females: Advise females of reproductive potential to use effective contraception during treatment with ELAHERE and for 7 months after the last dose.

8.4 Pediatric Use

Safety and effectiveness of ELAHERE have not been established in pediatric patients.

8.5 Geriatric Use

Of the 682 patients with epithelial ovarian cancer who were treated with ELAHERE across studies, 44% of patients were ≥65 years old. Grade ≥3 adverse reactions occurred in 51% of patients ≥65 years and in 45% <65 years. No clinically meaningful differences in efficacy or safety were observed between patients ≥65 years of age compared to younger patients.

Age does not have a clinically meaningful effect on the pharmacokinetics of ELAHERE [see Clinical Pharmacology (12.3)].

8.6 Renal Impairment

No dosage adjustment of ELAHERE is recommended for patients with mild to moderate renal impairment (CLcr 30 to 89 mL/min). The effect of severe renal impairment (CLcr 15 to < 30 mL/min) or end-stage renal disease on ELAHERE is unknown [see Clinical Pharmacology (12.3)].

8.7 Hepatic Impairment

Avoid use of ELAHERE in patients with moderate or severe hepatic impairment (total bilirubin >1.5 ULN).

No dosage adjustment of ELAHERE is recommended for patients with mild hepatic impairment (total bilirubin ≤ULN and AST >ULN or total bilirubin >1 to 1.5 times ULN and any AST) [see Clinical Pharmacology (12.3)].

11 DESCRIPTION

Mirvetuximab soravtansine-gynx is a folate receptor alpha (FRα)-directed antibody-drug conjugate (ADC) consisting of three components: 1) an anti-FRα monoclonal antibody of IgG1 subtype 2) the small molecule anti-tubulin agent DM4 (a maytansine derivative) and 3) a linker, sulfo-SPDB (1-(2,5-dioxopyrrolidin-1-yl)oxy-1-oxo-4-(pyridin-2-yldisulfanyl)butane-2-sulfonic acid) that covalently attaches DM4 to the mirvetuximab antibody. Mirvetuximab soravtansine-gynx has an approximate molecular weight of 150 kDa. An average of 3.4 molecules of DM4 are attached to each antibody molecule. Mirvetuximab soravtansine-gynx is produced by chemical conjugation of the antibody and small molecule components. The antibody is produced by mammalian (Chinese hamster ovary) cells, and the small molecule components are produced by chemical synthesis.

Mirvetuximab soravtansine-gynx has the following structure:

ELAHERE (mirvetuximab soravtansine-gynx) injection is supplied as a sterile, preservative-free, clear to slightly opalescent, colorless solution containing 100 mg/20 mL of mirvetuximab soravtansine-gynx in single-dose vials. Each mL of solution contains 5 mg of mirvetuximab soravtansine-gynx, and glacial acetic acid (0.22 mg), polysorbate 20 (0.1 mg), sodium acetate (0.53 mg), sucrose (90 mg), and Water for Injection. The pH is approximately 5.0.

The ELAHERE vial stoppers are not made with natural rubber latex.

12 CLINICAL PHARMACOLOGY

12.1 Mechanism of Action

Mirvetuximab soravtansine-gynx is an antibody-drug conjugate (ADC). The antibody is a chimeric IgG1 directed against folate receptor alpha (FRα). The small molecule, DM4, is a microtubule inhibitor attached to the antibody via a cleavable linker. Upon binding to FRα, mirvetuximab soravtansine-gynx is internalized followed by intracellular release of DM4 via proteolytic cleavage. DM4 disrupts the microtubule network within the cell, resulting in cell cycle arrest and apoptotic cell death.

12.2 Pharmacodynamics

Exposure-Response Relationships

Higher exposure to mirvetuximab soravtansine-gynx was associated with higher overall response rates and longer median PFS and OS; higher exposure to mirvetuximab soravtansine-gynx was also associated with higher incidence of ocular adverse reactions as well as marginally increased peripheral neuropathy.

Cardiac Electrophysiology

At the approved recommended dose, ELAHERE did not cause large mean increases (>10 msec) in the QTc interval.

12.3 Pharmacokinetics

The pharmacokinetics were characterized in patients who received mirvetuximab soravtansine-gynx 0.16 mg/kg to 8.7 mg/kg adjusted ideal body weight (AIBW) (0.03 times to 1.4 times the approved recommended dose of 6 mg/kg AIBW), unless otherwise noted.

Table 8 summarizes the exposure parameters of mirvetuximab soravtansine-gynx, unconjugated DM4, and its metabolite S-methyl-DM4 following administration after the first cycle (3-weeks). Peak mirvetuximab soravtansine-gynx concentrations were observed near the end of intravenous infusion, while peak unconjugated DM4 concentrations were observed on the second day after administration and the peak S-methyl-DM4 concentrations were observed approximately 3 days after administration. Steady state concentrations of mirvetuximab soravtansine-gynx, DM4, and S-methyl-DM4 were reached after one 3-week cycle. Accumulation of the mirvetuximab soravtansine-gynx, DM4, and S-methyl-DM4 was minimal following multiple cycles.

Table 8: Exposure Parameters of Mirvetuximab Soravtansine-gynx, Unconjugated DM4, and S-methyl DM4 After First Cycle at a Dosage of 6 mg/kg
 | Mirvetuximab Soravtansine-gynx Mean (±SD) | Unconjugated DM4 Mean (±SD) | S-methyl-DM4 Mean (±SD)
Cmax | 137.3 (±62.3) µg/mL | 4.1 (±2.3) ng/mL | 7.0 (±6.8) ng/mL
AUCtau | 20.6 (±6.8) h*mg/mL | 530 (±245) h*ng/mL | 1848 (±1585) h*ng/mL

Cmax = maximum concentration, AUCtau = area under the concentration vs. time curve over the dosing interval (21 days).

Distribution

The mean (±SD) steady state volume of distribution of mirvetuximab soravtansine-gynx was 2.6 (±2.9) L.

Human plasma protein binding of DM4 and S-methyl DM4 was >99%, in vitro.

Elimination

For mirvetuximab soravtansine-gynx, total plasma clearance (mean [CV%]) of was 19 mL/hour (52%) and the mean terminal phase half-life after the first dose was 4.8 days leading to a steady state at approximately 24 days.

For the unconjugated DM4, the total plasma clearance (mean [CV%]) was 14 L/hour (31%) and the mean terminal phase half-life was 2.8 days.

For S-methyl-DM4, the total plasma clearance (mean [CV%]) was 4.3 L/hour (64%) and the mean terminal phase half-life was 5 days.

Metabolism

The monoclonal antibody portion of mirvetuximab soravtansine-gynx is expected to be metabolized into small peptides by catabolic pathways. Unconjugated DM4 and S-methyl-DM4 undergo metabolism by CYP3A4. In human plasma, DM4 and S-methyl DM4 were identified as the main circulating metabolites, accounting for approximately 0.4% and 1.4% of mirvetuximab soravtansine-gynx AUC, respectively.

Excretion

S-methyl DM4 and DM4-sulfo-SPDB-lysine were detected in urine within 24 hours of infusion as the main metabolites.

Specific Populations

No clinically significant differences in the pharmacokinetics of mirvetuximab soravtansine-gynx were observed based on age (32 to 89 years), race (White, Black, or Asian), body weight (36 to 136 kg), mild hepatic impairment (total bilirubin ≤ULN and any AST >ULN or total bilirubin >1 to 1.5 times ULN and any AST), or mild to moderate renal impairment (CLcr 30 to 89 mL/min).

The pharmacokinetics of mirvetuximab soravtansine-gynx in patients with moderate to severe hepatic impairment (total bilirubin >1.5 ULN with any AST) or severe renal impairment (CLcr 15 to 30 mL/min) is unknown.

Drug Interaction Studies

Clinical Studies and Model Informed Approaches

No clinical studies to evaluate the drug-drug interaction potential of mirvetuximab soravtansine-gynx were conducted.

There were no differences in exposure between patients who received concomitant weak or moderate CYP3A4 inhibitors or P-glycoprotein (P-gp) inhibitors and those who did not.

In Vitro Studies

Cytochrome P450 (CYP) Enzymes: Unconjugated DM4 is a time-dependent inhibitor of CYP3A4. Unconjugated DM4 and S-methyl DM4 are not inhibitors of CYP1A2, CYP2B6, CYP2C8, CYP2C9, CYP2C19, CYP2D6, or CYP3A. DM4 and S-methyl DM4 are not inducers of CYP1A2, CYP2B6, or CYP3A4.

Transporter Systems: Unconjugated DM4 and S-methyl DM4 are substrates of P-gp but are not inhibitors of P-gp.

12.6 Immunogenicity

The observed incidence of anti-drug antibodies (ADA), including neutralizing antibody, is highly dependent on the sensitivity and specificity of the assay. Differences in assay methods preclude meaningful comparisons of the incidence of ADAs in the studies described below with the incidence of ADAs to mirvetuximab soravtansine-gynx in other studies.

With a median treatment duration of 4.4 months in Studies 0416, 0417, 0401, and 0403, in patients with epithelial ovarian, fallopian tube, or primary peritoneal cancer who received mirvetuximab soravtansine-gynx at 6 mg/kg AIBW intravenously every 3 weeks, 9% (57/626) of patients developed anti-mirvetuximab soravtansine-gynx antibodies. Neutralizing antibodies were detected in 47% (27/57) of patients who were ADA-positive.

No clinically meaningful difference was observed in the trough concentrations of mirvetuximab soravtansine-gynx between ADA-positive and ADA-negative patients. Anti-mirvetuximab soravtansine-gynx antibody formation was associated with a higher incidence of infusion-related reactions [see Adverse Reactions (6.1)]. The effect of anti-drug antibodies on effectiveness has not been fully characterized. Based on limited data, the presence of anti-mirvetuximab soravtansine-gynx antibodies may be associated with decreased efficacy in ADA-positive patients when compared to ADA-negative patients.

13 NONCLINICAL TOXICOLOGY

13.1 Carcinogenesis, Mutagenesis, Impairment of Fertility

Carcinogenicity studies have not been conducted with mirvetuximab soravtansine-gynx or DM4.

DM4 and the metabolite, S-methyl DM4, were clastogenic in the in vivo rat bone marrow micronucleus study. DM4 and S-methyl DM4 were not mutagenic in the bacterial reverse mutation (Ames) assay.

Fertility studies have not been conducted with mirvetuximab soravtansine-gynx or DM4.

14 CLINICAL STUDIES

Study 0416

The efficacy of ELAHERE was evaluated in Study 0416 (MIRASOL, NCT04209855), a multicenter, open-label, active-controlled, randomized, two-arm, trial in patients (n=453) with FRα positive, platinum-resistant epithelial ovarian, fallopian tube, or primary peritoneal cancer. Patients were permitted to receive up to three prior lines of systemic therapy. The trial enrolled patients whose tumors were positive for FRα expression as determined by the VENTANA FOLR1 (FOLR1-2.1) RxDx Assay. Patients were excluded if they had corneal disorders, ocular conditions requiring ongoing treatment, Grade >1 peripheral neuropathy, or noninfectious interstitial lung disease.

Patients were randomized (1:1) to receive ELAHERE 6 mg/kg (based on adjusted ideal body weight) as an intravenous infusion every 3 weeks or investigator’s choice of chemotherapy (paclitaxel, pegylated liposomal doxorubicin [PLD], or topotecan) until disease progression or unacceptable toxicity. Tumor response assessments occurred every 6 weeks for the first 36 weeks and every 12 weeks thereafter. Randomization was stratified by the following factors: number of prior lines of therapy (1 vs. 2 vs. 3) and chemotherapy (paclitaxel vs. PLD vs. topotecan) chosen prior to randomization.

The major efficacy outcome measures were investigator-assessed progression-free survival (PFS), confirmed overall response rate (ORR), and overall survival (OS). PFS and ORR were evaluated according to Response Evaluation Criteria in Solid Tumors (RECIST), version 1.1.

The median age was 63 years (range: 29 to 88); 66% were White, 12% were Asian, 3% were Black or African American, and 18% did not have race reported. Six percent of patients were Hispanic or Latino. Nearly all patients had an ECOG PS of 0 (55%) or 1 (44%). Fourteen percent of patients had received 1 prior line of systemic therapy, 39% of patients had received 2 prior lines of systemic therapy, and 47% of patients had received 3 prior lines of systemic therapy. Thirty-seven percent of patients received prior systemic therapy for platinum-resistant disease. Sixty-two percent of patients received prior bevacizumab and 55% had received a prior PARP inhibitor.

ELAHERE demonstrated a statistically significant improvement in PFS, ORR, and OS for patients randomized to ELAHERE as compared with chemotherapy.

Efficacy results for Study 0416 are summarized in Table 9 and Figures 1 and 2.

Table 9: Efficacy Results in Study 0416
 | ELAHERE n=227 | Chemotherapy* n=226
Progression-free survival (PFS)
Number (%) of patients with events | 176 (78) | 166 (73)
Median, months (95% CI) | 5.6 (4.3, 5.9) | 4.0 (2.9, 4.5)
Hazard ratio (95% CI) | 0.65 (0.52, 0.81)
p-valuea | <0.0001
Overall Survival (OS)
Number (%) of patients with events | 90 (40) | 114 (50)
Median, months (95% CI) | 16.5 (14.5, 24.6) | 12.7 (10.9, 14.4)
Hazard Ratio (95% CI) | 0.67 (0.50, 0.88)
p-valuea | 0.0046
Confirmed overall response rate (ORR)
Number of patients with measurable disease at baseline | 225 | 224
ORR (95% CI) | 42% (36, 49) | 16% (12, 22)
Complete response | 5% | 0%
Partial response | 37% | 16%
p-valueb | <0.0001

* Chemotherapy: paclitaxel, PLD, or topotecan.

a Two-sided p-value based on stratified log-rank test.

b Two-sided p-value based upon Cochran-Mantel-Haenszel (CMH) test.

Figure 1: Kaplan-Meier Curve for Progression-free Survival in Study 0416

Figure 2: Kaplan-Meier Curve for Overall Survival in Study 0416

Study 0417

The efficacy of ELAHERE was evaluated in Study 0417 (SORAYA, NCT04296890), a single-arm trial of patients with FRα positive, platinum-resistant epithelial ovarian, fallopian tube, or primary peritoneal cancer (n=106). Patients were permitted to receive up to three prior lines of systemic therapy. All patients were required to have received prior bevacizumab. The trial enrolled patients whose tumors were positive for FRα expression as determined by the VENTANA FOLR1 (FOLR1-2.1) RxDx Assay. Patients were excluded if they had corneal disorders, ocular conditions requiring ongoing treatment, Grade >1 peripheral neuropathy, or noninfectious interstitial lung disease.

Patients received ELAHERE 6 mg/kg (based on adjusted ideal body weight) as an intravenous infusion every 3 weeks until disease progression or unacceptable toxicity. Tumor response assessments occurred every 6 weeks for the first 36 weeks and every 12 weeks thereafter.

The major efficacy outcome measures were investigator-assessed overall response rate (ORR) and duration of response (DOR) evaluated according to Response Evaluation Criteria in Solid Tumors (RECIST), version 1.1.

The efficacy evaluable population included 104 patients with platinum-resistant disease, who had measurable disease, and received at least one dose of ELAHERE. In these 104 patients, the median age was 62 years (range: 35 to 85); 96% were White, 2% were Asian, and 2% did not have race reported. Two percent of patients were Hispanic or Latino. All patients had an ECOG PS of 0 (57%) or 1 (43%). Ten percent of patients had received 1 prior line of systemic therapy, 39% of patients had received 2 prior lines of systemic therapy, and 50% of patients had received 3 prior lines of systemic therapy. All patients had received prior bevacizumab and 47% had received a prior PARP inhibitor.

Efficacy results for Study 0417 are summarized in Table 10.

Table 10: Efficacy Results in Study 0417
 | ELAHERE (N=104)
Confirmed Overall Response Ratea (95% CI) | 32% (23, 42)
Complete response rate | 5%
Partial response rate | 27%
Duration of Response | N=33
Median duration of response, months (95% CI) | 6.9 (5.6, 9.7)

a Investigator assessment.

Response assessment results using independent radiology review were consistent with investigator assessment.

15 REFERENCES

^1“OSHA Hazardous Drugs.” OSHA. http://www.osha.gov/SLTC/hazardousdrugs/index.html

16 HOW SUPPLIED/STORAGE AND HANDLING

How Supplied

Each ELAHERE (mirvetuximab soravtansine-gynx) injection carton (NDC 72903-853-01) contains:

- One single-dose vial containing 100 mg of mirvetuximab soravtansine-gynx in 20 mL (5 mg/mL) of clear to slightly opalescent, colorless sterile solution.

Storage and Handling

Store ELAHERE vials upright in a refrigerator at 2°C to 8°C (36°F to 46°F) until the time of preparation in the original carton to protect from light.

Do not freeze or shake.

ELAHERE is a hazardous drug. Follow applicable special handling and disposal procedures^1.

17 PATIENT COUNSELING INFORMATION

Advise the patient to read the FDA-approved patient labeling (Medication Guide).

Ocular Disorders

Inform patients about the need for eye exams before and during treatment with ELAHERE.

Advise patients to contact their healthcare provider promptly if they experience any visual changes. Advise patients to use steroid eye drops and artificial tear substitutes [see Dosage and Administration (2.3) and Warnings and Precautions (5.1)].

Pneumonitis

Advise patients to immediately report new or worsening respiratory symptoms [see Dosage and Administration (2.3) and Warnings and Precautions (5.2)].

Embryo-Fetal Toxicity

Advise pregnant women and females of reproductive potential of the potential risk to a fetus. Advise female patients to inform their healthcare provider of a known or suspected pregnancy [see Use in Specific Populations (5.4, 8.1, 8.3)].

Advise females of reproductive potential to use effective contraception during treatment with ELAHERE and for 7 months after the last dose [see Use in Specific Populations (8.1, 8.3)].

Lactation

Advise women not to breastfeed during treatment with ELAHERE and for 1 month after the last dose [see Use in Specific Populations (8.2)].

Manufactured by:
AbbVie Inc.
North Chicago, IL 60064, USA
U.S. License 1889

©2025 AbbVie Inc. All rights reserved.
ELAHERE and its design are trademarks of ImmunoGen, Inc., an AbbVie company.
752962-02

MEDICATION GUIDE
ELAHERE® (el-ah-HERE)
(mirvetuximab soravtansine-gynx)
injection, for intravenous use

What is the most important information I should know about ELAHERE?
ELAHERE can cause serious side effects, including:

- Eye problems. Eye problems are common with ELAHERE and can also be severe. Tell your healthcare provider right away if you develop any eye problems during treatment with ELAHERE, including blurred vision, dry eyes, sensitivity to light, eye pain, eye redness, or new or worsening vision changes.
  - Your healthcare provider will send you to see an eye care professional to check your eyes before you start treatment with ELAHERE, during treatment with ELAHERE, and as needed for any worsening signs and symptoms of eye problems.
  - Your healthcare provider will prescribe steroid eye drops and lubricating eye drops before you start and during your treatment with ELAHERE. You should use eye drops as directed by your healthcare provider.
  - Do not wear contact lenses throughout your treatment with ELAHERE unless you are told to use them by your healthcare provider.

See “What are the possible side effects of ELAHERE?” for more information about side effects.

What is ELAHERE?
ELAHERE is a prescription medicine used to treat adults with folate receptor-alpha positive ovarian cancer, fallopian tube cancer, or primary peritoneal cancer who:

- have not responded to or are no longer responding to treatment with platinum-based chemotherapy, and
- have received 1 to 3 prior types of chemotherapy.

Your healthcare provider will perform a test to make sure that ELAHERE is right for you.
It is not known if ELAHERE is safe and effective in children.

Before receiving ELAHERE, tell your healthcare provider about all of your medical conditions, including if you:

- have vision or eye problems.
- have numbness or tingling in your hands or feet.
- have liver problems.
- are pregnant or plan to become pregnant. ELAHERE can harm your unborn baby. Tell your healthcare provider right away if you become pregnant or think you may be pregnant during treatment with ELAHERE.
  Patients who are able to become pregnant:
  - Your healthcare provider should do a pregnancy test before you start treatment with ELAHERE.
  - You should use an effective birth control (contraception) during treatment and for 7 months after your last dose of ELAHERE.
- are breastfeeding or plan to breastfeed. It is not known if ELAHERE passes into your breast milk. Do not breastfeed during treatment and for 1 month after your last dose of ELAHERE.

Tell your healthcare provider about all the medicines you take, including prescription and over-the-counter medicines, vitamins, and herbal supplements. Taking certain other medicines during treatment with ELAHERE may cause side effects.

How will I receive ELAHERE?

- ELAHERE will be given to you by infusion into your vein (intravenous or IV).
- Before each dose of ELAHERE you will receive medicines to help prevent infusion related reactions, nausea, and vomiting.
- ELAHERE is usually given every 3 weeks (21-day cycle). Your healthcare provider will decide how many cycles you need.

What are the possible side effects of ELAHERE?
ELAHERE can cause serious side effects, including:

- See “What is the most important information I should know about ELAHERE?”
- Lung problems (pneumonitis). ELAHERE can cause severe or life-threatening inflammation of the lungs that may lead to death. Tell your healthcare provider right away if you get new or worsening symptoms, including trouble breathing, shortness of breath, cough, or chest pain.
- Peripheral neuropathy. Nerve problems called peripheral neuropathy are common with ELAHERE and can also be severe. Your healthcare provider will monitor you for signs and symptoms of nerve problems. Tell your healthcare provider if you get new or worsening numbness, tingling, burning sensation or pain in your hands or feet or muscle weakness.

The most common side effects and abnormal labs of ELAHERE include:

- increased liver enzymes in the blood

- decreased platelets

- feeling tired

- decreased magnesium level in the blood

- blurred vision

- dry eye

- nausea

- constipation

- diarrhea

- vomiting

- stomach-area (abdominal) pain

- decreased albumin level in the blood

- changes in the cornea (part of the eye)

- decreased appetite

- peripheral neuropathy

- muscle, bone, or joint pain

- decreased red or white blood cell counts

Your healthcare provider may change your dose of ELAHERE, delay treatment, or completely stop treatment if you have certain side effects.
These are not all of the possible side effects of ELAHERE.
Call your doctor for medical advice about side effects. You may report side effects to FDA at 1-800-FDA-1088.

General information about the safe and effective use of ELAHERE.
Medicines are sometimes prescribed for purposes other than those listed in a Medication Guide. If you would like more information about ELAHERE, talk with your healthcare provider. You can ask your pharmacist or healthcare provider for information about ELAHERE that is written for healthcare professionals.

What are the ingredients in ELAHERE?
Active ingredient: mirvetuximab soravtansine-gynx
Inactive ingredients: glacial acetic acid, polysorbate 20, sodium acetate, sucrose, Water for Injection.
Manufactured by: AbbVie Inc., North Chicago, IL 60064, USA
U.S. License 1889
©2025 AbbVie Inc. All rights reserved.
ELAHERE and its design are trademarks of ImmunoGen, Inc., an AbbVie company.
752962-02
For more information, go to www.elahere.com or call 1-833-ELAHERE.

This Medication Guide has been approved by the U.S. Food and Drug Administration. Revised 07/2025

PACKAGE LABEL

NDC: 72903-853-01
Rx Only
ELAHERE®
mirvetuximab soravtansine-gynx
Injection
100mg/20ml
(5mg/ml)
For Intravenous Infusion after
Dilution in 5% Dextrose Injection, USP
Single-dose vial.
Discard unused portion
Warning: Hazardous Drug
Dispense the enclosed
Medication Guide to each patient.
abbvie